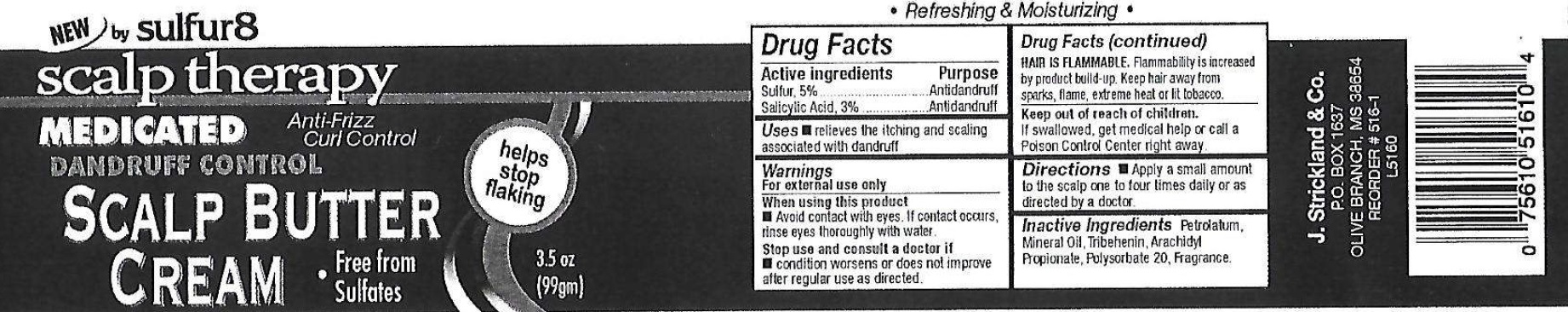 DRUG LABEL: Sulfur 8 Scalp Therapy Medicated Dandruff Control Scalp Butter Cream
NDC: 12022-035 | Form: OINTMENT
Manufacturer: J. Strickland and Co.
Category: otc | Type: HUMAN OTC DRUG LABEL
Date: 20231021

ACTIVE INGREDIENTS: SULFUR 50 mg/1 g; SALICYLIC ACID 30 mg/1 g
INACTIVE INGREDIENTS: PETROLATUM; MINERAL OIL; TRIBEHENIN; ARACHIDYL PROPIONATE; POLYSORBATE 20

Sulfur 8 Scalp Therapy Medicated Dandruff Control Scalp Butter Cream

Active Ingredient

Sulfur, 5%

Salicylic Acid, 3%

Purpose

Antidandruff

Use

- relieves the itching and scaling associated with dandruff

Warnings

For external use only

When using this product

avoid contact with eyes. If contact occurs rinse eyes thoroughly with water.

Stop use and consult a doctor if

- condition worsens or does not improve after regular use as directed.
- HAIR IS FLAMMABLE. Flammability is increased by product build-up. Keep hair away from sparks, flame, extreme heat or lit tobacco.

Keep out of reach of children.

If swallowed, get medical help or call a Poison Control Center right away.

Directions

- Apply a small amount to the scalp one to four times daily or as directed by a doctor.

Inactive Ingredients

Petrolatum, Mineral Oil, Tribehenin, Arachidyl Propionate, Polysorbate 20, Fragrance